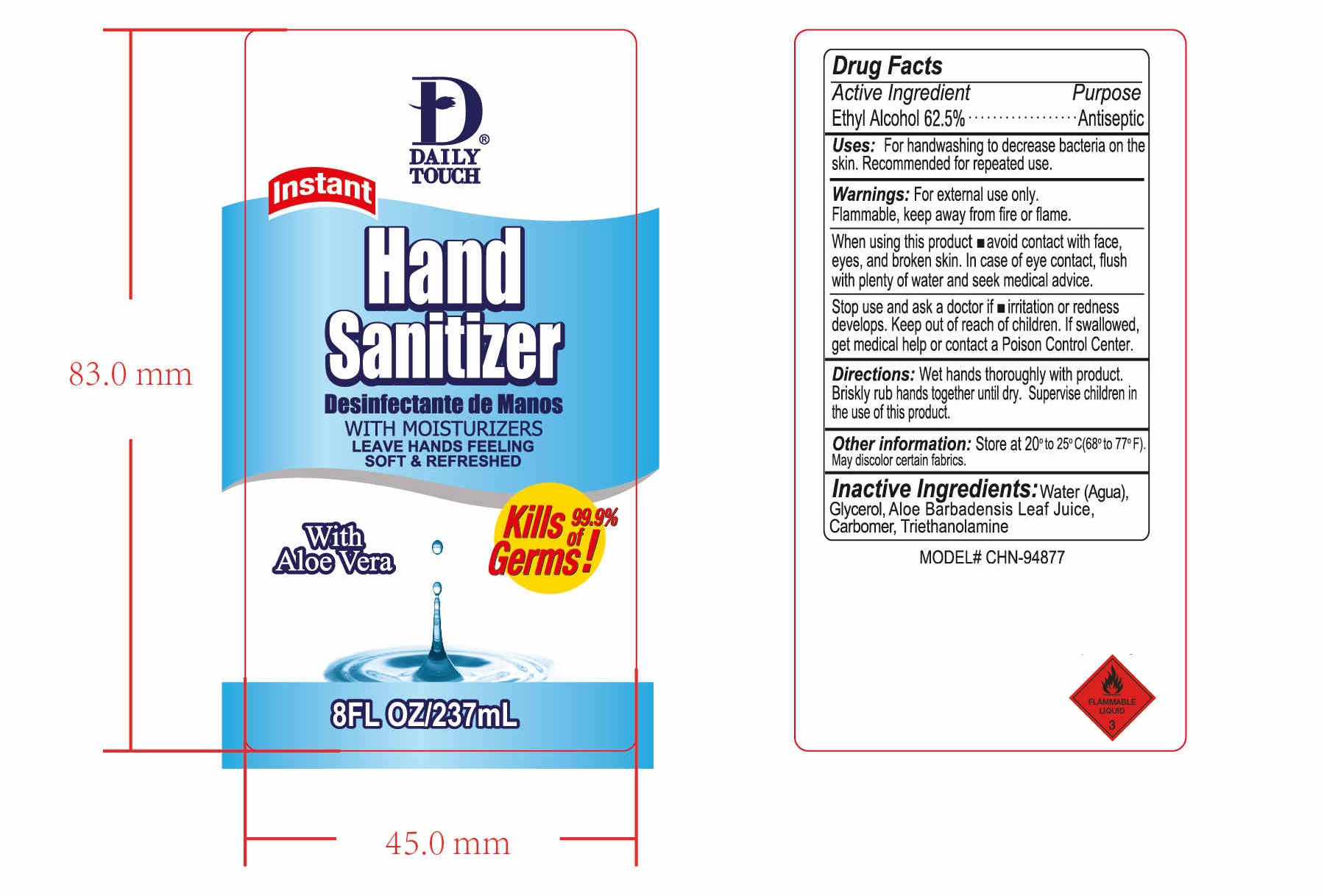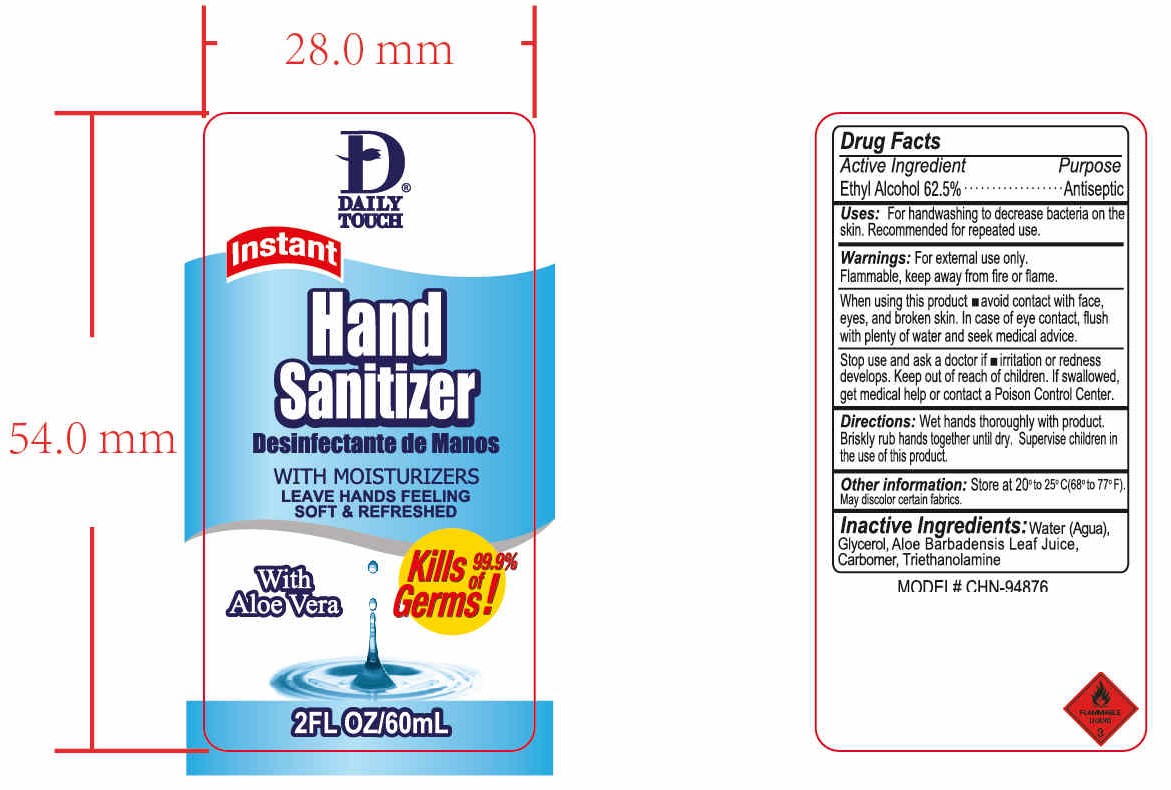 DRUG LABEL: HAND SANITIZER
NDC: 47993-250 | Form: GEL
Manufacturer: NINGBO JIANGBEI OCEAN STAR TRADING CO.,LTD
Category: otc | Type: HUMAN OTC DRUG LABEL
Date: 20201104

ACTIVE INGREDIENTS: ALCOHOL 62.5 g/112 mL
INACTIVE INGREDIENTS: ALOE VERA LEAF; WATER; GLYCERIN; CARBOMER 940; TRIETHANOLAMINE BENZOATE

47993-250

Active ingredients

Ethyl Alcohol 62.5%

PURPOSE

Antiseptic

Uses：

For hand washing to decrease bacteria on the skin. Recommended for repeated use.

Warnings:

For external use only. Flammable, keep away from fire and flame.

when using this product

- avoid contact with the face, eyes, and broken skin. In case of eye contact, flush with plenty of water and seek medical advice

Stop use and ask a doctor if

- irritation or redness develops. Keep out of reach of children. If swallowed，get medical help or contact Poison Control Center.

Keep out of reach of children. If swallowed，get medical help or contact Poison Control Center.

Directions:

Wet hands thoroughly with product. Briskly rub hands together until dry. Supervise children in the use of this product.

Other information：

Store at 20℃to25℃（68℉to77℉). May discolor certain fabrics.

Inactive Ingredients:

Water(Aqua),Glycerol,Aloe Barbadensis Leaf Juice,Carbomer,Triethanolamine